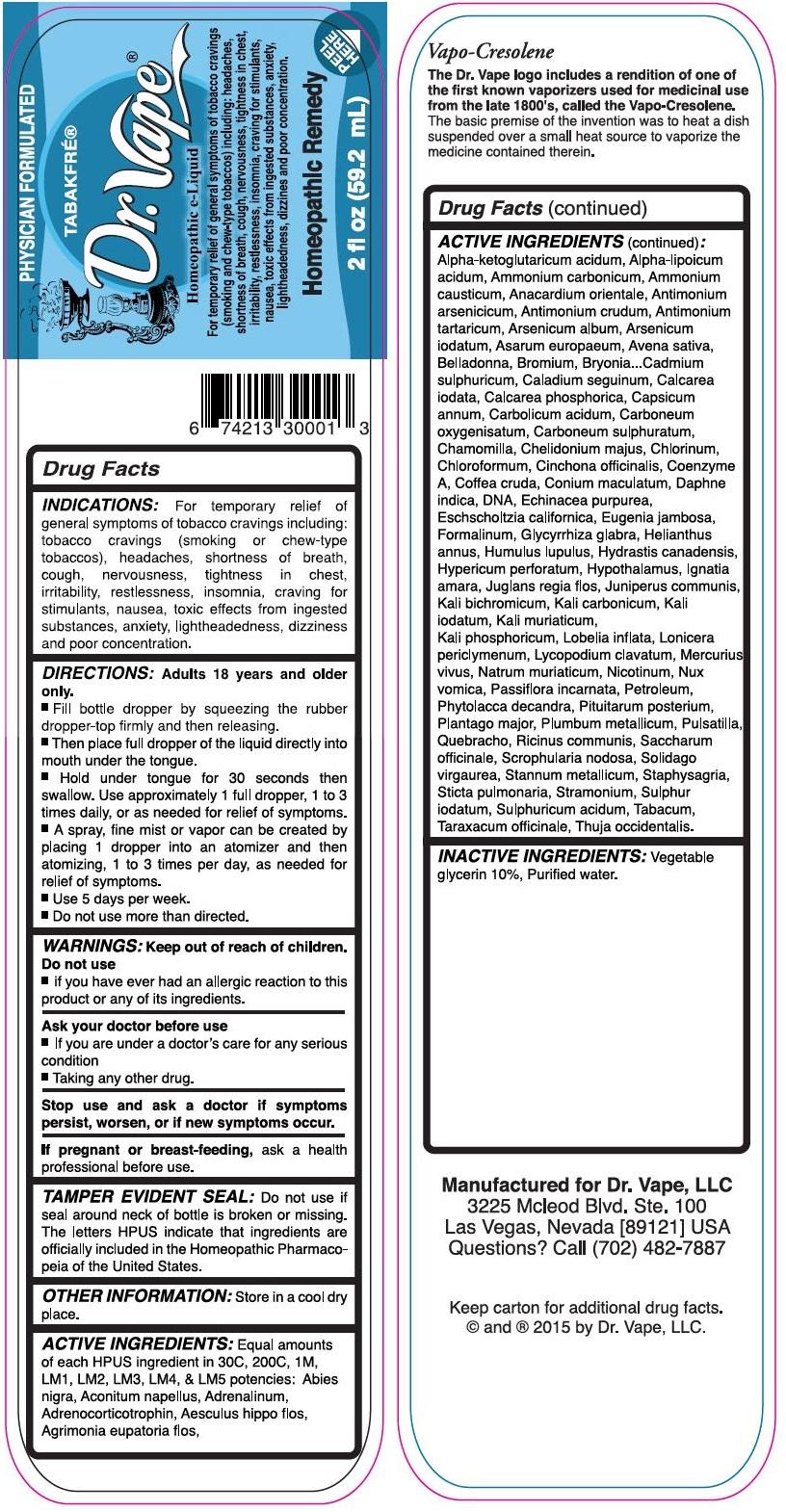 DRUG LABEL: Tabakfre
NDC: 70034-001 | Form: SOLUTION
Manufacturer: Primal Earth LLC
Category: homeopathic | Type: HUMAN OTC DRUG LABEL
Date: 20151020

ACTIVE INGREDIENTS: ACONITUM NAPELLUS 30 [hp_C]/60 mL; .ALPHA.-LIPOIC ACID, (+/-)- 30 [hp_C]/60 mL; AGRIMONIA EUPATORIA FLOWER 30 [hp_C]/60 mL; AMMONIA 30 [hp_C]/60 mL; AMMONIUM CARBONATE 30 [hp_C]/60 mL; ANTIMONY ARSENATE 30 [hp_C]/60 mL; ANTIMONY POTASSIUM TARTRATE 30 1/60 mL; ANTIMONY TRISULFIDE 30 1/60 mL; ARABICA COFFEE BEAN 30 1/60 mL; ARSENIC TRIIODIDE 30 1/60 mL; ARSENIC TRIOXIDE 30 1/60 mL; ASARUM EUROPAEUM 30 1/60 mL; ASPIDOSPERMA QUEBRACHO-BLANCO BARK 30 1/60 mL; ATROPA BELLADONNA 30 1/60 mL; AVENA SATIVA FLOWERING TOP 30 1/60 mL; BOS TAURUS HYPOTHALAMUS 30 1/60 mL; BROMINE 30 1/60 mL; CALCIUM IODIDE 30 1/60 mL; CAPSICUM 30 1/60 mL; CARBON DISULFIDE 30 1/60 mL; CARBON MONOXIDE 30 1/60 mL; CHELIDONIUM MAJUS 30 1/60 mL; CHLORINE 30 1/60 mL; CHLOROFORM 30 1/60 mL; CINCHONA OFFICINALIS BARK 30 1/60 mL; COENZYME A 30 1/60 mL; CONIUM MACULATUM FLOWERING TOP 30 1/60 mL; CORTICOTROPIN 30 1/60 mL; DAPHNE ODORA BARK 30 1/60 mL; DATURA STRAMONIUM 30 1/60 mL; DELPHINIUM STAPHISAGRIA SEED 30 1/60 mL; DIEFFENBACHIA SEGUINE 30 1/60 mL; ECHINACEA PURPUREA 30 1/60 mL; EPINEPHRINE 30 1/60 mL; ESCHSCHOLZIA CALIFORNICA 30 1/60 mL; FORMALDEHYDE 30 1/60 mL; GLYCYRRHIZA GLABRA 30 1/60 mL; GOLDENSEAL 30 1/60 mL; HELIANTHUS ANNUUS FLOWERING TOP 30 1/60 mL; HERRING SPERM DNA 30 1/60 mL; HOPS 30 1/60 mL; HORSE CHESTNUT 30 1/60 mL; HYPERICUM PERFORATUM 30 1/60 mL; JUGLANS REGIA FLOWERING TOP 30 1/60 mL; JUNIPERUS COMMUNIS WHOLE 30 1/60 mL; LEAD 30 1/60 mL; LIQUID PETROLEUM 30 1/60 mL; LOBARIA PULMONARIA 30 1/60 mL; LOBELIA INFLATA 30 1/60 mL; LONICERA PERICLYMENUM FLOWERING TWIG 30 1/60 mL; LYCOPODIUM CLAVATUM SPORE 30 1/60 mL; MATRICARIA RECUTITA 30 1/60 mL; MERCURY 30 1/60 mL; NICOTINE 30 1/60 mL; OXOGLURIC ACID 30 1/60 mL; PASSIFLORA INCARNATA FLOWERING TOP 30 1/60 mL; PHENOL 30 1/60 mL; PHYTOLACCA AMERICANA ROOT 30 1/60 mL; PICEA MARIANA RESIN 30 1/60 mL; PLANTAGO MAJOR 30 1/60 mL; POTASSIUM CARBONATE 30 1/60 mL; POTASSIUM CHLORIDE 30 1/60 mL; POTASSIUM DICHROMATE 30 1/60 mL; POTASSIUM IODIDE 30 1/60 mL; POTASSIUM PHOSPHATE, DIBASIC 30 1/60 mL; PULSATILLA PRATENSIS 30 [hp_C]/60 mL; RICINUS COMMUNIS SEED 30 1/60 mL; SCROPHULARIA NODOSA 30 1/60 mL; SEMECARPUS ANACARDIUM JUICE 30 1/60 mL; SODIUM CHLORIDE 30 1/60 mL; SOLIDAGO VIRGAUREA FLOWERING TOP 30 1/60 mL; STRYCHNOS IGNATII SEED 30 1/60 mL; STRYCHNOS NUX-VOMICA SEED 30 1/60 mL; SUCROSE 30 1/60 mL; SULFUR IODIDE 30 1/60 mL; SULFURIC ACID 30 1/60 mL; SUS SCROFA PITUITARY GLAND 30 1/60 mL; SYZYGIUM JAMBOS SEED 30 1/60 mL; TARAXACUM OFFICINALE 30 1/60 mL; THUJA OCCIDENTALIS LEAFY TWIG 30 1/60 mL; TIN 30 1/60 mL; TOBACCO LEAF 30 1/60 mL; TRIBASIC CALCIUM PHOSPHATE 30 1/60 mL
INACTIVE INGREDIENTS: CADMIUM SULFATE; GLYCERIN; WATER

ACTIVE INGREDIENT

Equal amounts of each HPUS ingredient in 30C, 200C, 1M, LM1, LM2, LM3, LM4, & LM5 Potencies:

Abies nigra, Aconitum napellus, Adrenalinum, Adrenocorticotrophin, Aesculus hippo flos, Agrimonia eupatoria flos, Alpha-katoglutaricum acidum, Alpha -lipoicum, acidum, Ammonium carbonicum, Ammonium arsenicicum, Antimonium crudum, Antimonium lartaricum, Arsenicum album, Arsenicum ioatum, Asarum europaeum, Avena sativa, Bel adonna, Bromium, Bryonia, Cadmium sulphuricum, Caladium seguinum, Calcarea iodata, Calcarea phosphorica, Capsicum annum, Carbolicum acidum, Carboneum oxygenisatum, Carboneum sulphuratum, Chamomilla, Chelidonium majus, chlorinum,Chloroformum, Cinchona officinalis, Coenzyme A. Colfea cruda, Conium maculatum, Daphne indica, DNA, Echinacea purpurea, Eschscholtzia californica, Eugenia jambosa, Formalinum, Glycyrrhiza glabra, Helianthus annus, Humulus lupulus, Hydrastis canadensis, Hypericum perforatum, Hypthalamus, Ignatia amara, juglans regia flos, Juniperus communis, Kali bichromicum, Kali Carbonicum, Kali iodatum, Kali muriaticum, Kali phophoricum, Lobelia inflata, Lonicera periclymenum, Lycopodium clavatum, Mercurius vivus, Natrum muriaticum, Nicotinum, Nux vornica, Passiflora incarnata, Petroleum, Phytolacca decandra, Pituitarum posterium, Plantago major, Plumbum metlicum, Pulsatilla, Quebracho, Ricinus cmmunis, Saccharum officinale, Scrophularia nodosa, Solidago virgaurea, Stannum metallicum, Staphysagria,Sticta pulmonaria, Stramonium, Sulphur iodatum, Sulphuricum acidum, Tabacum, Taraxacum officinale, Thuja occidentalis.

OTC - PURPOSE SECTION

For temporary relief of general symptoms of tobacco cravings including: tobacco cravings (smoking or chew-type tobaccos), headaches, shortness of breath, cough, nervousness, tightness in chest, irritability, restlessness, insomnia, craving for stimulants, nausea, toxic effcts from ingested substances, enxiety, lightheadedness, dizziness and poor concentration.

OTC - KEEP OUT OF REACH OF CHILDREN SECTION

Keep out of reach of children.

Indications and Usage

For temporary relief of general symptoms of tobacco cravings including: tobacco cravings (smoking or chew type tobaccos), headaches, shortness of breath, cough, nervousness, tightness in chest, irritability, restlessness, insomnia, craving for stimulants, nausa, toxic effects from ingested substances, anxiety, lightheadedness, dizziness and poor concentration.

DOSAGE & ADMINISTRATION SECTION

Fill bottle dropper by squeezing the rubber dropper-top firmly and then releasing.

Place full dropper of the liquid directly into mouth under the tongue.

Hold under tongue for 30 seconds then swallow. use approximately 1 full dropper, 1 to 3 times daily, or as needed for relief of symptoms.

A spray, fine mist or vapor can be created by placing 1 dropper into an atomizer and ten atomizing, 1 to 3 times per day, as needed for relief of symptoms.

Use 5 days per week.

Do not use more than directed.

WARNINGS

Do not use if you have ever had an allergic reaction to this product or any of its ingredients.

Ask your doctor befgore use

- if you are under a doctor's care for any serious condition
- taking any other drug

Stop use and ask a doctor if symptoms persist, worsen, or if new symptoms occur.

If pregnant or breast-feeding, ask a health professional before use.

INACTIVE INGREDIENT SECTION

Vegetable glycerin 10%, Purified Water.